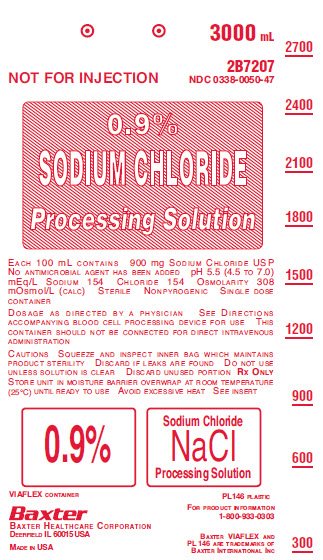 DRUG LABEL: Sodium Chloride
NDC: 0338-0050 | Form: SOLUTION
Manufacturer: Baxter Healthcare Corporation
Category: prescription | Type: HUMAN PRESCRIPTION DRUG LABEL
Date: 20140725

ACTIVE INGREDIENTS: SODIUM CHLORIDE 900 mg/100 mL
INACTIVE INGREDIENTS: WATER

0.9% Sodium Chloride Processing Solution
in Flexible Plastic Container
Not for injection

DESCRIPTION

Sodium Chloride Processing Solution is a sterile, nonpyrogenic solution in single dose container for use in blood cell processing devices. It contains no antimicrobial agents. Composition, osmolarity, pH, and ionic concentration are shown in Table 1.

Table 1
0.9% Sodium Chloride Processing Solution | Size (mL) | Composition (g/L) | Osmolarity (mOsmol/L) (calc) | pH | Ionic Concentration (mEq/L)
0.9% Sodium Chloride Processing Solution | Size (mL) | Sodium Chloride, USP (NaCl) | Osmolarity (mOsmol/L) (calc) | pH | Sodium | Chloride
0.9% Sodium Chloride Processing Solution | 3000 | 9 | 308 | 5.5 (4.5 to 7.0) | 154 | 154

The plastic container is fabricated from a specially formulated polyvinyl chloride (PL 146 Plastic). The amount of water that can permeate from inside the container into the overwrap is insufficient to affect the solution significantly. Solutions in contact with the plastic container can leach out certain of its chemical components in very small amounts within the expiration period, e.g., di-2-ethylhexylphthalate (DEHP), up to 5 parts per million. However, the safety of the plastic has been confirmed in tests in animals according to USP biological tests for plastic containers as well as by tissue culture toxicity studies.

CLINICAL PHARMACOLOGY

0.9% Sodium Chloride Processing Solution has value as a physiological blood cell processing aid.

INDICATIONS AND USAGE

0.9% Sodium Chloride Processing Solution is indicated in processing blood cells.

See directions accompanying blood cell processing device for complete instructions for use.

CONTRAINDICATIONS

None known

WARNINGS

This container should not be connected for direct intravenous administration.

The contents of an opened container should be used promptly to minimize the possibility of bacterial growth or pyrogen formation. Discard the unused portion of processing solution.

PRECAUTIONS

Careful review and understanding of the use of this solution in conjunction with blood cell processing equipment is essential.

Pregnancy

Teratogenic Effects

Pregnancy Category C.

Animal reproduction studies have not been conducted with 0.9% Sodium Chloride Processing Solution. It is also not known whether 0.9% Sodium Chloride Processing Solution can cause fetal harm when administered to a pregnant woman or can affect reproduction capacity. 0.9% Sodium Chloride Processing Solution should be given to a pregnant woman only if clearly needed.

Pediatric Use

Safety and effectiveness in pediatric patients have not been established.

Do not administer unless solution is clear and seal is intact.

ADVERSE REACTIONS

None known

DOSAGE AND ADMINISTRATION

As directed by a physician. See directions accompanying blood cell processing device.

Processing Solutions should be inspected visually for particulate matter and discoloration prior to use.

HOW SUPPLIED

0.9% Sodium Chloride Processing Solution in Flexible Plastic Container is available as follows:

Code | Size (mL) | NDC
2B7207 | 3000 | 0338-0050-47

Exposure of pharmaceutical products to heat should be minimized. Avoid excessive heat. It is recommended the product be stored at room temperature (25º C); brief exposure up to 40º C does not adversely affect the product.

To Open

Tear overwrap down side at slit and remove solution container. Visually inspect the container. If the outlet port protector is damaged, detached, or not present, discard container as solution path sterility may be impaired. Some opacity of the plastic due to moisture absorption during the sterilization process may be observed. This is normal and does not affect the solution quality or safety. The opacity will diminish gradually. Check for minute leaks by squeezing inner bag firmly. If leaks are found, discard solution as sterility may be impaired.

Preparation for Use

1. Suspend container from eyelet support.
2. Remove plastic protector from outlet port at bottom of container.
3. Attach to blood cell processing device. Refer to complete directions accompanying blood cell processing device.

Baxter Healthcare Corporation
Deerfield, IL 60015 USA

Printed in USA

©Copyright 1983, 1990, 1995, Baxter Healthcare Corporation. All rights
reserved.

07-19-73-065

Rev. May 2014

BAXTER, AND PL 146 ARE TRADEMARKS OF BAXTER INTERNATIONAL INC.

PACKAGE/LABEL PRINCIPAL DISPLAY PANEL

3000 mL

2B7207
NDC 0338-0050-47

NOT FOR INJECTION

0.9%
SODIUM CHLORIDE
Processing Solution

EACH 100 mL CONTAINS 900 mg SODIUM CHLORIDE USP
NO ANTIMICROBIAL AGENT HAS BEEN ADDED pH 5.5 (4.5 TO 7.0)
mEq/L SODIUM 154 CHLORIDE 154 OSMOLARITY 308
mOsmol/L (CALC) STERILE NONPYROGENIC SINGLE DOSE
CONTAINER

DOSAGE AS DIRECTED BY A PHYSICIAN SEE DIRECTIONS
ACCOMPANYING BLOOD CELL PROCESSING DEVICE FOR USE THIS
CONTAINER SHOULD NOT BE CONNECTED FOR DIRECT INTRAVENOUS
ADMINISTRATION

CAUTIONS SQUEEZE AND INSPECT INNER BAG WHICH MAINTAINS
PRODUCT STERILITY DISCARD IF LEAKS ARE FOUND DO NOT USE
UNLESS SOLUTION IS CLEAR DISCARD UNUSED PORTION RX ONLY
STORE UNIT IN MOISTURE BARRIER OVERWRAP AT ROOM TEMPERATURE
(25°C) UNTIL READY TO USE AVOID EXCESSIVE HEAT SEE INSERT

0.9%
Sodium Chloride
NaCl
Processing Solution

VIAFLEX CONTAINER

PL146 PLASTIC
FOR PRODUCT INFORMATION

1-800-933-0303

Baxter Logo
Baxter Healthcare Corporation
Deerfield, IL 60015 USA

Made in USA

Baxter VIAFLEX and
PL 146 are trademarks of
Baxter International Inc